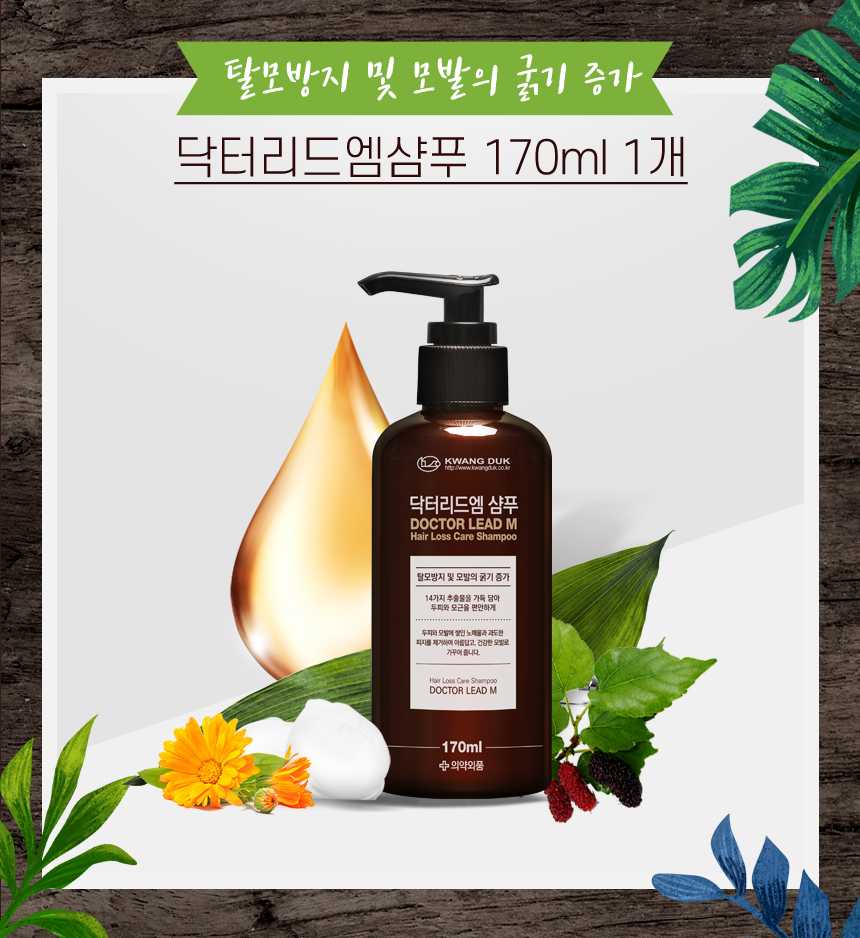 DRUG LABEL: DOCTOR LEAD M
NDC: 71838-0003 | Form: SHAMPOO
Manufacturer: Kwang Duk Sin Yak Co., Ltd.
Category: otc | Type: HUMAN OTC DRUG LABEL
Date: 20180126

ACTIVE INGREDIENTS: SALICYLIC ACID 0.25 g/100 mL
INACTIVE INGREDIENTS: NIACINAMIDE; PANTHENOL

Drug Facts

ACTIVE INGREDIENT

salicylic acid

INACTIVE INGREDIENT

water, glycerin, dimethicone copolyol, citric acid, etc

PURPOSE

Prevents hair loss, thickens hair root and enables improvement on your scalp.

keep out of reach of the children

INDICATIONS AND USAGE

apply the appropriate amount to the scalp, then shampoo and wash away

WARNINGS

Cautions :

1. When you use this product and find any of following problems, stop using it. if you keep using it despite the problem, the symptom will get worse, so you will have to go see a dermatologist.

- During use, if you have red spots, swelling, itching, or any other stimuli.

- if the applied region has any problem above for direct light.

2. Do not use the product on wound or dermatitis. 3.Attentive points for storage and treatment :

- Store it in the place where infants or children cannot touch

- do not store it where it has either high or low temperature or there is direct light.

DOSAGE AND ADMINISTRATION

for external use only